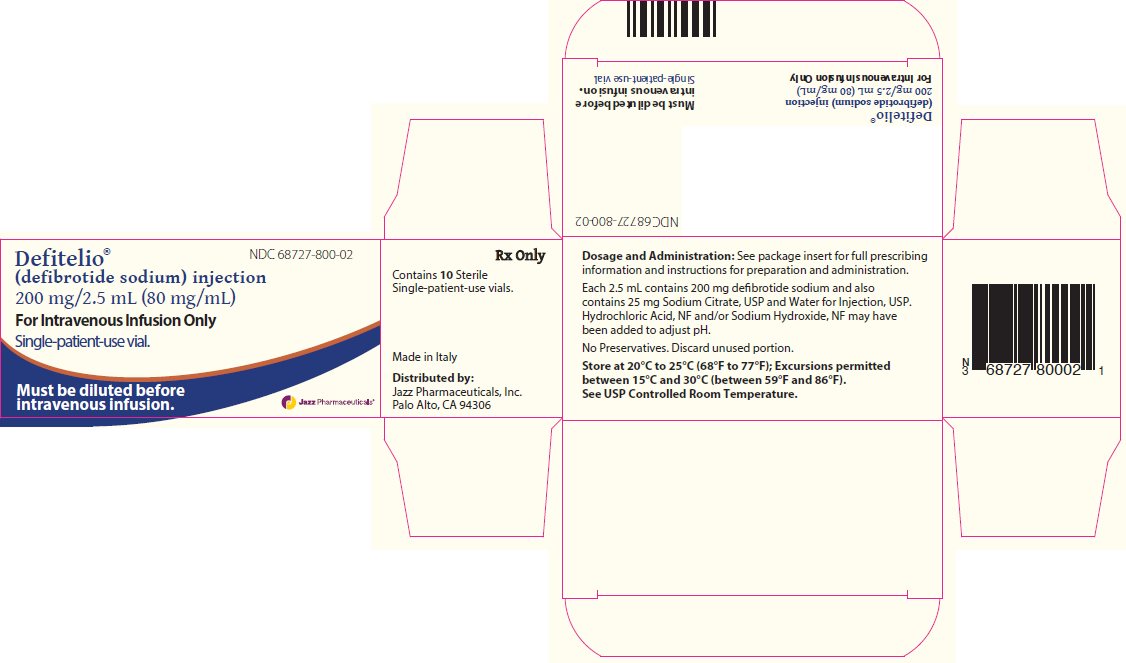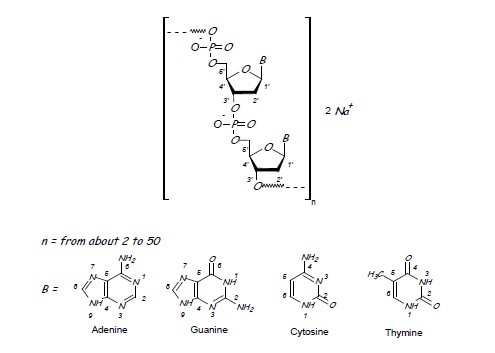 DRUG LABEL: DEFITELIO
NDC: 68727-800 | Form: INJECTION, SOLUTION
Manufacturer: Jazz Pharmaceuticals, Inc.
Category: prescription | Type: HUMAN PRESCRIPTION DRUG LABEL
Date: 20250701

ACTIVE INGREDIENTS: DEFIBROTIDE SODIUM 80 mg/1 mL
INACTIVE INGREDIENTS: TRISODIUM CITRATE DIHYDRATE; WATER; HYDROCHLORIC ACID; SODIUM HYDROXIDE

HIGHLIGHTS OF PRESCRIBING INFORMATION

These highlights do not include all the information needed to use DEFITELIO safely and effectively. See full prescribing information for DEFITELIO.
DEFITELIO (defibrotide sodium) injection, for intravenous use
Initial U.S. Approval: 2016

1 INDICATIONS AND USAGE

DEFITELIO is indicated for the treatment of adult and pediatric patients with hepatic veno-occlusive disease (VOD), also known as sinusoidal obstruction syndrome (SOS), with renal or pulmonary dysfunction following hematopoietic stem-cell transplantation (HSCT). (1)

2 DOSAGE AND ADMINISTRATION

- Administer DEFITELIO 6.25 mg/kg every 6 hours given as a 2-hour intravenous infusion. (2.1)
- Treat for a minimum of 21 days. If after 21 days signs and symptoms of VOD have not resolved, continue treatment until resolution. (2.1)

3 DOSAGE FORMS AND STRENGTHS

Injection: 200 mg/2.5 mL (80 mg/mL) in a single-patient-use vial. (3)

4 CONTRAINDICATIONS

- Concomitant administration with systemic anticoagulant or fibrinolytic therapy. (4)
- Known hypersensitivity to DEFITELIO or to any of its excipients. (4)

5 WARNINGS AND PRECAUTIONS

- Hemorrhage: Monitor patients for bleeding. Withhold or discontinue DEFITELIO if significant bleeding occurs. (2.3, 5.1)
- Hypersensitivity Reactions: If severe or life threatening allergic reaction occurs, discontinue DEFITELIO, treat according to standard of care, and monitor until signs and symptoms resolve. (2.3, 5.2)

6 ADVERSE REACTIONS

The most common adverse reactions (incidence ≥10% and independent of causality) with DEFITELIO treatment were hypotension, diarrhea, vomiting, nausea, and epistaxis. (6.1)

To report SUSPECTED ADVERSE REACTIONS, contact Jazz Pharmaceuticals, Inc. at 1-800-520-5568 or FDA at 1-800-FDA-1088 or www.fda.gov/medwatch.

7 DRUG INTERACTIONS

- DEFITELIO may enhance the activity of antithrombotic/fibrinolytic drugs. (7)

FULL PRESCRIBING INFORMATION

1 INDICATIONS AND USAGE

DEFITELIO is indicated for the treatment of adult and pediatric patients with hepatic veno-occlusive disease (VOD), also known as sinusoidal obstruction syndrome (SOS), with renal or pulmonary dysfunction following hematopoietic stem-cell transplantation (HSCT).

2 DOSAGE AND ADMINISTRATION

2.1 Recommended Dosage

The recommended dosage of DEFITELIO for adult and pediatric patients is 6.25 mg/kg every 6 hours given as a 2‑hour intravenous infusion. The dose should be based on patient’s baseline body weight, defined as the patient’s weight prior to the preparative regimen for HSCT.

Administer DEFITELIO for a minimum of 21 days. If after 21 days signs and symptoms of hepatic VOD have not resolved, continue DEFITELIO until resolution of VOD or up to a maximum of 60 days.

2.2 Administration Instructions

- DEFITELIO must be diluted prior to infusion [see Dosage and Administration (2.4)].
- Prior to administration of DEFITELIO, confirm that the patient is not experiencing clinically significant bleeding and is hemodynamically stable on no more than one vasopressor [see Warnings and Precautions (5.1)].
- Administer DEFITELIO by constant intravenous infusion over a 2-hour period.
- Administer the diluted DEFITELIO solution using an infusion set equipped with a 0.2 micron in-line filter. Flush the intravenous administration line (peripheral or central) with 5% Dextrose Injection, USP or 0.9% Sodium Chloride Injection, USP immediately before and after administration.
- Do not co‑administer DEFITELIO and other intravenous drugs concurrently within the same intravenous line.

2.3 Treatment Modification

Treatment modification, including temporary or permanent discontinuation of DEFITELIO, should follow the recommendations in Table 1.

Table 1: Treatment Modifications for Toxicity or Invasive Procedures

Event | Recommended Action
Hypersensitivity Reaction
Severe or life-threatening (anaphylaxis) | 1. Discontinue DEFITELIO permanently; do not resume treatment.
Bleeding
Persistent, severe or potentially life-threatening | 1. Withhold DEFITELIO. 2. Treat the cause of bleeding and give supportive care as clinically indicated. 3. Consider resuming treatment (at the same dose and infusion volume) when bleeding has stopped and the patient is hemodynamically stable.
Recurrent significant bleeding | 1. Discontinue DEFITELIO permanently; do not resume treatment.
Invasive Procedures
 | 1. There is no known reversal agent for the profibrinolytic effects of DEFITELIO. Discontinue DEFITELIO infusion at least 2 hours prior to an invasive procedure. 2. Resume DEFITELIO treatment after the procedure as soon as any procedure-related risk of bleeding is resolved.

2.4 Preparation Instructions

Dilute DEFITELIO in 5% Dextrose Injection, USP or 0.9% Sodium Chloride Injection, USP to a concentration of 4 mg/mL to 20 mg/mL. Administer the diluted solution over 2 hours.

Vials contain no antimicrobial preservatives and are intended for a single-patient-use only. Partially used vials should be discarded. Use the diluted DEFITELIO solution within 4 hours if stored at room temperature or within 24 hours if stored under refrigeration. Up to four doses of DEFITELIO solution may be prepared at one time, if refrigerated.

Preparation Instructions:

- Determine the dose (mg) and number of vials of DEFITELIO based on the individual patient’s baseline weight (weight prior to the preparative regimen for HSCT).
- Calculate the volume of DEFITELIO needed, withdraw this amount from the vial(s) and add it to the infusion bag containing 0.9% Sodium Chloride Injection or 5% Dextrose Injection for each dose to make a final concentration of 4 mg/mL to 20 mg/mL.
- Gently mix the solution for infusion.
- Parenteral drug products should be inspected visually for particulate matter and discoloration prior to administration, whenever solution and container permit. Only clear solutions without visible particles should be used. Depending on the type and amount of diluent, the color of the diluted solution may vary from colorless to light yellow.

3 DOSAGE FORMS AND STRENGTHS

Injection: 200 mg/2.5 mL (80 mg/mL) of defibrotide sodium as a clear, light yellow to brown solution in a single-patient-use glass vial.

4 CONTRAINDICATIONS

The use of DEFITELIO is contraindicated in the following conditions:

- Concomitant administration with systemic anticoagulant or fibrinolytic therapy [see Warnings and Precautions (5.1)]
- Known hypersensitivity to DEFITELIO or to any of its excipients [see Warnings and Precautions (5.2)]

5 WARNINGS AND PRECAUTIONS

5.1 Hemorrhage

DEFITELIO increased the activity of fibrinolytic enzymes in vitro, and it may increase the risk of bleeding in patients with VOD after hematopoietic stem-cell transplantation (HSCT). Do not initiate DEFITELIO in patients with active bleeding. Monitor patients for signs of bleeding. If patients on DEFITELIO develop bleeding, discontinue DEFITELIO, treat the underlying cause, and provide supportive care until the bleeding has stopped [see Dosage and Administration (2.3)].

Concomitant use of DEFITELIO and a systemic anticoagulant or fibrinolytic therapy (not including use for routine maintenance or reopening of central venous lines) may increase the risk of bleeding. Discontinue anticoagulants and fibrinolytic agents prior to DEFITELIO treatment, and consider delaying the start of DEFITELIO administration until the effects of the anticoagulant have abated [see Contraindications (4)].

5.2 Hypersensitivity Reactions

Hypersensitivity reactions have occurred in less than 2% of patients treated with DEFITELIO. These reactions include rash, urticaria and angioedema. One case of an anaphylactic reaction was reported in a patient who had previously received DEFITELIO. Monitor patients for hypersensitivity reactions, especially if there is a history of previous exposure. If a severe hypersensitivity reaction occurs, discontinue DEFITELIO, treat according to the standard of care, and monitor until symptoms resolve [see Dosage and Administration (2.3)].

6 ADVERSE REACTIONS

The following adverse reactions are discussed in greater detail in other sections of the labeling:

- Hemorrhage [see Warnings and Precautions (5.1)]
- Hypersensitivity Reactions [see Warnings and Precautions (5.2)]

6.1 Clinical Trials Experience

Because clinical trials are conducted under widely varying conditions, adverse reaction rates observed in the clinical trials of a drug cannot be directly compared to rates in the clinical trials of another drug and may not reflect the rates observed in practice.

The safety of DEFITELIO was determined in 176 adult and pediatric patients with hepatic VOD with pulmonary and/or renal dysfunction following HSCT who were treated with DEFITELIO 6.25 mg/kg every 6 hours [see Clinical Studies (14)]. Patients were excluded from these trials if at time of study entry they had significant acute bleeding, active grades B-D graft-versus-host disease, or a requirement for multiple vasopressors to provide blood pressure support. For the purposes of adverse event recording in the clinical trials, events were not required to be reported if they were related to the hepatic VOD, or if they were expected to occur after hematopoietic stem-cell transplantation (HSCT), unless they were serious or Grade 4-5.

The median age of the safety population was 25 years (range: 1 month to 72 years), and 63% were ≥17 years of age. A total of 60% of patients were male, 78% were white, 89% had undergone allogeneic HSCT, and the underlying diagnosis was acute leukemia for 43%. At study entry, 13% were dialysis dependent and 18% were ventilator dependent. DEFITELIO was administered for a median of 21 days (range: 1 to 83 days).

Information about adverse reactions resulting in permanent discontinuation of DEFITELIO was available for 102 patients, and 35 (34%) of these patients had an adverse reaction with permanent discontinuation. Adverse reactions leading to permanent discontinuation included pulmonary alveolar hemorrhage in 5 (5%) patients; pulmonary hemorrhage, hypotension, catheter site hemorrhage, and multi-organ failure, each in 3 (3%) patients; and cerebral hemorrhage and sepsis, each in 2 (2%) patients.

Information about adverse reactions of any grade was available for all 176 patients. The most common adverse reactions (incidence ≥10% and independent of causality) were hypotension, diarrhea, vomiting, nausea, and epistaxis. The most common serious adverse reactions (incidence ≥5% and independent of causality) were hypotension (11%) and pulmonary alveolar hemorrhage (7%). Hemorrhage events of any type and any grade were reported for 104 (59%) of the patients, and the events were grade 4-5 in 35 (20%).

Table 2 presents adverse reactions independent of causality ≥10% any grade or Grade 4/5 ≥2% reported in patients treated with DEFITELIO.

Table 2: Adverse Reactionsa ≥10% or Grade 4-5 Adverse Reactions ≥2%

 | DEFITELIO; (n=176)
Adverse Reaction a | Any grade | Grade 4-5b
Hypotension | 65 (37%) | 12 (7%)
Diarrhea | 43 (24%) | 0
Vomiting | 31 (18%) | 0
Nausea | 28 (16%) | 0
Epistaxis | 24 (14%) | 0
Pulmonary alveolar hemorrhage | 15 (9%) | 12 (7%)
Gastrointestinal hemorrhage | 15 (9%) | 5 (3%)
Sepsis | 12 (7%) | 9 (5%)
Graft versus host disease | 11 (6%) | 7 (4%)
Lung infiltration | 10 (6%) | 5 (3%)
Pneumonia | 9 (5%) | 5 (3%)
Pulmonary hemorrhage | 7 (4%) | 4 (2%)
Infection | 6 (3%) | 4 (2%)
Hemorrhage intracranial | 5 (3%) | 4 (2%)
Hyperuricemia | 4 (2%) | 4 (2%)
Cerebral hemorrhagec | 3 (2%) | 3 (2%)

a Excludes events considered to be due to the underlying disease: multi-organ failure, veno-occlusive disease, respiratory failure, renal failure, and hypoxia

b Adverse reactions considered life-threatening or fatal

c Cerebral hemorrhage has been included in the table due to clinical relevance

7 DRUG INTERACTIONS

Antithrombotic Agents

DEFITELIO may enhance the pharmacodynamic activity of antithrombotic/fibrinolytic drugs such as heparin or alteplase. Concomitant use of DEFITELIO with antithrombotic or fibrinolytic drugs is contraindicated because of an increased risk of hemorrhage [see Contraindications (4)].

8 USE IN SPECIFIC POPULATIONS

8.1 Pregnancy

Risk Summary

There are no available data on DEFITELIO use in pregnant women. When administered to pregnant rabbits during the period of organogenesis at doses that were comparable to the recommended human dose based on body surface area, defibrotide sodium decreased the number of implantations and viable fetuses. Advise pregnant women of the potential risk of miscarriage.

The estimated background risk of major birth defects and miscarriage for the indicated population is unknown. In the U.S. general population, the estimated background risks of major birth defects and miscarriage in clinically recognized pregnancies are 2-4% and 15-20%, respectively.

Data

Animal Data

Embryo-Fetal toxicity assessment was attempted in rats and rabbits, but was not possible because of high maternal mortality, abortion, and fetal resorption at all doses. Pregnant rats were administered defibrotide sodium from gestational day (GD) 6 to 15 at 0, 240, 1200, and 4800 mg/kg/day by continuous intravenous infusion over 24 hours or at 60, 120, and 240 mg/kg/day by 2-hour infusions 4 times per day. Pregnant rabbits were administered defibrotide sodium at 0, 30, 60, or 120 mg/kg/day from GD 6 to 18 by 2-hour infusions 4 times per day.

In another study in pregnant rabbits, 3 separate subgroups of animals were treated with doses of 80 mg/kg/day defibrotide sodium administered by 2-hour infusions 4 times per day for 5 days each in a staggered manner during the organogenesis period. The dose of 80 mg/kg/day is approximately equivalent to the recommended clinical dose on a mg/m^2 basis. Subgroup 1 was dosed from GD 6 to 10, subgroup 2 was dosed from GD 10 to 14, and subgroup 3 was dosed from GD 14 to 18. An increased incidence of unilateral implantation was observed in defibrotide sodium-treated animals. Treatment with defibrotide sodium resulted in a decreased number of implantations and viable fetuses.

8.2 Lactation

Risk Summary

There is no information regarding the presence of DEFITELIO in human milk, the effects on the breastfed infant, or the effects on milk production. Because of the potential for serious adverse reactions, including bleeding in a breastfed infant, advise patients that breastfeeding is not recommended during treatment with DEFITELIO.

8.4 Pediatric Use

The safety and effectiveness of DEFITELIO have been established in pediatric patients. Use of DEFITELIO is supported by evidence from an adequate and well-controlled study and a dose finding study of DEFITELIO in adult and pediatric patients with VOD with evidence of renal or pulmonary dysfunction following HSCT. The clinical trials enrolled 66 pediatric patients in the following age groups: 22 infants (1 month up to less than 2 years), 30 children (2 years up to less than 12 years), and 14 adolescents (12 years to less than 17 years). The efficacy and safety outcomes were consistent across pediatric and adult patients in the clinical trials [see Adverse Reactions (6) and Clinical Studies (14)].

Juvenile Animal Toxicity Data

A juvenile toxicity study in 21-day-old rats was conducted with intravenous bolus administration of defibrotide sodium at 40, 150, or 320 mg/kg/day for 4 weeks. A delayed mean age of preputial separation was observed at all doses, suggesting a delay in onset of male puberty. The dose of 40 mg/kg/day is approximately 0.4 times the clinical dose on a mg/m^2 basis for a child. The relevance of this finding for the onset of male puberty in humans is unknown.

8.5 Geriatric Use

Clinical studies of DEFITELIO did not include sufficient numbers of subjects aged 65 and over to determine whether they respond differently from younger subjects. Other reported clinical experience has not identified differences in responses between the elderly and younger patients.

10 OVERDOSAGE

There are no known cases of overdose with DEFITELIO. There is no known antidote for DEFITELIO, and DEFITELIO is not dialyzable. If an overdose occurs, institute general supportive measures.

11 DESCRIPTION

Defibrotide sodium is an oligonucleotide mixture with profibrinolytic properties. The chemical name of defibrotide sodium is polydeoxyribonucleotide, sodium salt. Defibrotide sodium is a polydisperse mixture of predominantly single-stranded (ss) polydeoxyribonucleotide sodium salts derived from porcine intestinal tissue having a mean weighted molecular weight of 14-19 kDa, and a potency of 27-39 and 28-38 biological units per mg as determined by two separate assays measuring the release of a product formed by contact between defibrotide sodium, plasmin and a plasmin substrate. The primary structure of defibrotide sodium is shown below.

DEFITELIO (defibrotide sodium) injection is a clear, light yellow to brown, sterile, preservative-free solution in a single-patient-use vial for intravenous use. Each milliliter of the injection contains 80 mg of defibrotide sodium and 10 mg of Sodium Citrate, USP, in Water for Injection, USP. Hydrochloric Acid, NF, and/or Sodium Hydroxide, NF, may have been used to adjust pH to 6.8-7.8.

12 CLINICAL PHARMACOLOGY

12.1 Mechanism of Action

The mechanism of action of defibrotide sodium has not been fully elucidated. In vitro, defibrotide sodium enhances the enzymatic activity of plasmin to hydrolyze fibrin clots. Studies evaluating the pharmacological effects of defibrotide sodium on endothelial cells (ECs) were conducted primarily in the human microvascular endothelial cell line. In vitro, defibrotide sodium increased tissue plasminogen activator (t-PA) and thrombomodulin expression, and decreased von Willebrand factor (vWF) and plasminogen activator inhibitor‑1 (PAI-1) expression, thereby reducing EC activation and increasing EC‑mediated fibrinolysis. Defibrotide sodium protected ECs from damage caused by chemotherapy, tumor necrosis factor-α (TNF-α), serum starvation, and perfusion.

12.2 Pharmacodynamics

Cardiac Electrophysiology

At a dose 2.4 times the maximum recommended dose, DEFITELIO does not prolong the QTc interval to any clinically relevant extent.

PAI-1 Inhibition

Plasma concentrations of PAI-1 were assessed on an exploratory basis as a potential pharmacodynamic marker for efficacy in Study 2. PAI-1 is an inhibitor of t-PA and therefore of fibrinolysis. Mean PAI-1 levels on Days 7 and 14 were lower than those at baseline in patients with complete response (CR) and in those who were alive at Day+100, but this trend did not reach statistical significance. There were no statistically significant differences in mean PAI-1 levels by treatment or outcome.

12.3 Pharmacokinetics

Absorption

After intravenous administration, peak plasma concentrations of defibrotide sodium occur approximately at the end of each infusion.

Distribution

Defibrotide sodium is highly bound to human plasma proteins (average 93%) and has a volume of distribution of 8.1 to 9.1 L.

Elimination

Metabolism followed by urinary excretion is likely the main route of elimination. The estimated total clearance was 3.4 to 6.1 L/h. The elimination half-life of defibrotide sodium is less than 2 hours. Similar plasma concentration profiles were observed in VOD patients after initial and multiple-dose administration of 6.25 mg/kg every 6 hours for 5 days. Therefore, no accumulation is expected following multiple-dose administration.

Metabolism

Though the precise pathway of defibrotide sodium degradation in plasma in vivo is largely unknown, it has been suggested that nucleases, nucleotidases, nucleosidases, deaminases, and phosphorylases metabolize polynucleotides progressively to oligonucleotides, nucleotides, nucleosides, and then to the free 2'-deoxyribose sugar, purine and pyrimidine bases.

The biotransformation of defibrotide sodium was investigated in vitro by incubation with human hepatocytes from donors of different ages and showed that defibrotide sodium does not undergo appreciable metabolism by human hepatocyte cells.

Excretion

After administration of 6.25 mg/kg to 15 mg/kg doses of DEFITELIO as 2-hour infusions, approximately 5-15% of the total dose was excreted in urine as defibrotide sodium, with the majority excreted during the first 4 hours.

Specific Populations

Age: Pediatric Population

Insufficient PK data were collected in pediatric patients to draw conclusions.

Renal Impairment

The safety, tolerability, and pharmacokinetics of 6.25 mg/kg as 2-hour intravenous infusions of DEFITELIO were evaluated in patients with Hemodialysis-dependent End Stage Renal Disease (ESRD) during hemodialysis and on days off dialysis, and in patients with severe renal disease or ESRD not requiring dialysis. Defibrotide sodium was not removed by hemodialysis, which had no notable effect on plasma clearance of defibrotide sodium. Terminal half-lives were consistently less than 2 hours, and there was no accumulation of defibrotide sodium following repeated dosing. Defibrotide sodium exposure (AUC) in patients with severe renal impairment or ESRD was 50% to 60% higher than that observed in matched healthy subjects. Peak concentration (Cmax) was 35% to 37% higher following single- and multiple-dose administration of defibrotide sodium.

Drug Interactions

Pharmacokinetic drug-drug interactions are unlikely at therapeutic dose. Data from in vitro studies using human biomaterial demonstrate that defibrotide sodium does not induce (CYP1A2, CYP2B6, CYP3A4, UGT1A1) or inhibit (CYP1A2, CYP2B6, CYP3A4, CYP2C8, CYP2C9, CYP2C19, CYP2D6, UGT1A1, UGT2B7) the major drug metabolizing enzymes and is not a substrate or inhibitor of the major drug uptake transporters (OAT1, OAT3, OCT1, OCT2, OATP1B1, OATP1B3) or efflux transporters (P-gp and BCRP).

There is some evidence (animal studies, ex vivo human plasma, and healthy volunteers) that defibrotide sodium may enhance the pharmacodynamic activity of heparin and alteplase [see Drug Interactions (7)].

13 NONCLINICAL TOXICOLOGY

13.1 Carcinogenesis, Mutagenesis, Impairment of Fertility

No carcinogenicity studies have been conducted with intravenous administration of defibrotide sodium.

Defibrotide sodium was not mutagenic in vitro in a bacterial reverse mutation assay (Ames assay). Defibrotide sodium was not clastogenic in an in vitro chromosomal aberrations assay in Chinese hamster ovary cells or an in vivo micronucleus assay conducted in bone marrow from rats administered defibrotide sodium by intravenous infusion.

Studies of fertility were not conducted with defibrotide sodium administered by the intravenous route. In repeat dose general toxicology studies, when defibrotide sodium was administered intravenously to rats and dogs for up to 13 weeks, there were no effects on male or female reproductive organs.

13.2 Animal Toxicology and/or Pharmacology

In the 13-week toxicity studies in rats and dogs, intravenous administration of defibrotide sodium transiently prolonged activated partial thromboplastin time (APTT) at 1200 and 4800 mg/kg/day administered as a continuous infusion in rats and at 300 and 1600 mg/kg/day administered in 2-hour infusions 4 times daily in dogs. Prothrombin time (PT) was also transiently increased at 4800 mg/kg/day in rats. These findings were observed at doses at least 6 times higher on a mg/m^2 basis than the clinical dose of 25 mg/kg/day. The effects on APTT and PT may be due to direct effects on coagulation based on the dose-dependent response observed.

14 CLINICAL STUDIES

The efficacy of DEFITELIO was investigated in three studies: two prospective clinical trials (Study 1 and Study 2), and an expanded access study (Study 3).

Study 1 enrolled 102 adult and pediatric patients in the DEFITELIO treatment group with a diagnosis of VOD according to the following criteria (bilirubin of at least 2 mg/dL and at least two of the following findings: hepatomegaly, ascites, and weight gain greater than 5% by Day+21 post-HSCT) with an associated diagnosis of multi-organ dysfunction (pulmonary, renal, or both) by Day+28 post-HSCT. DEFITELIO was administered to the treatment group at a dose of 6.25 mg/kg infused every 6 hours for a minimum of 21 days and continued until patient was discharged from the hospital. Patients enrolled in the DEFITELIO treatment group were not permitted to receive concomitant medications such as heparin, warfarin, or alteplase because of an increased risk of bleeding.

Study 2 included adult and pediatric patients with a diagnosis of hepatic VOD and multi-organ dysfunction following HSCT, with 75 patients treated with DEFITELIO at a dose of 6.25 mg/kg infused every 6 hours. The planned minimum duration of treatment was 14 days. The treatment could be continued until signs of hepatic VOD resolved.

Study 3 is an expanded access program for DEFITELIO for the treatment of adult and pediatric patients with hepatic VOD. The efficacy of defibrotide was evaluated in 351 patients who had received a HSCT and developed hepatic VOD with renal or pulmonary dysfunction. All patients received DEFITELIO at a dose of 6.25 mg/kg infused every 6 hours.

Baseline demographic information and details for patients treated in these studies are provided below in Table 3.

Table 3: Baseline Demographics of Patients Treated with DEFITELIO at 6.25 mg/kg Every 6 Hours

Data Source | Study 1 | Study 2 | Study 3
Design | Prospective | Prospective | Expanded Access Study
Number of patients | 102 | 75 | 351
Median age (years); (range) | 21 years; (<1, 72) | 32 years; (<1, 61) | 15 years; (<1, 69)
Age, n(%); < 17 years; ≥ 17 years | 44 (43%); 58 (57%) | 22 (29%); 53 (71%) | 189 (54%); 162 (46%)
Race, n(%); White; Black/African American; Asian; Other | 77 (75%); 6 (6%); 4 (4%); 15 (15%) | 61 (81%); 6 (8%); 2 (3%); 6 (8%) | 237 (68%); 21 (6%); 15 (4%); 78 (22%)
Gender, n(%); Male; Female | 64 (63%); 38 (37%) | 41 (55%); 34 (45%) | 184 (52%); 167 (48%)
Median number of days on treatment (days); (range) | 21.5 days; (1,58) | 19.5 days; (3,83) | 21.0 daysa; (1,93)
Type of graft, n(%); Allograft; Autograft | 90 (88%); 12 (12%) | 67 (89%); 8 (11%) | 317 (90%); 34 (10%)
Ventilator or Dialysis Dependent at Study Entry, n(%) | 34 (33%) | 8 (11%) | 149 (42%)

a Duration of treatment from first dose to last dose is presented because days without treatment were not captured for the expanded access study.

The efficacy of DEFITELIO was based on survival at Day + 100 after HSCT. In Study 1, the survival rate was 38% (95% CI: 29%, 48%) at 100 days after transplantation. In Study 2 the survival rate was 44% (95% CI: 33%, 55%) at 100 days after transplantation. In Study 3, the Day + 100 survival was 45% (95% CI: 40%, 51%).

Based on published reports and analyses of patient level data for individuals with hepatic VOD with renal or pulmonary dysfunction who received supportive care or interventions other than DEFITELIO, the expected Day +100 survival rates are 21% to 31%.

16 HOW SUPPLIED/STORAGE AND HANDLING

DEFITELIO (defibrotide sodium) injection is supplied in a single-patient-use, clear glass vial as a clear, light yellow to brown, sterile, preservative-free solution for intravenous infusion. Each vial (NDC 68727-800-01) contains 200 mg/2.5 mL (at a concentration of 80 mg/mL) of defibrotide sodium.

Each carton of DEFITELIO (defibrotide sodium) injection (NDC 68727-800-02) contains 10 vials.

Store DEFITELIO (defibrotide sodium) injection at 20°C-25°C (68°F-77°F); excursions permitted between 15°C to 30°C (59°F to 86°F) (see USP controlled room temperature).

17 PATIENT COUNSELING INFORMATION

- Hemorrhage: Advise patients and caregivers that DEFITELIO may increase the risk of bleeding (hemorrhage). Instruct patients to immediately report any signs or symptoms suggestive of hemorrhage (unusual bleeding, easy bruising, blood in urine or stool, headache, confusion, slurred speech, or altered vision) [see Warnings and Precautions (5.1)].
- Hypersensitivity Reactions: Ask patients if they have been treated with defibrotide sodium previously. Instruct patients on the risk of allergic reactions, including anaphylaxis. Describe the symptoms of allergic reactions, including anaphylaxis, and instruct the patient to seek medical attention immediately if they experience such symptoms [see Warnings and Precautions (5.2)].

PACKAGE/LABEL PRINCIPAL DISPLAY PANEL

This product's label may have been updated. For full prescribing information, please visit labels.fda.gov.

Distributed by:

Jazz Pharmaceuticals, Inc.
Palo Alto, CA 94306

Protected by U.S. Patent Nos. 11,085,043, 11,236,328 and 11,746,348

DEFITELIO® is a registered trademark of Jazz Pharmaceuticals plc or its subsidiaries.
© 2025 Jazz Pharmaceuticals